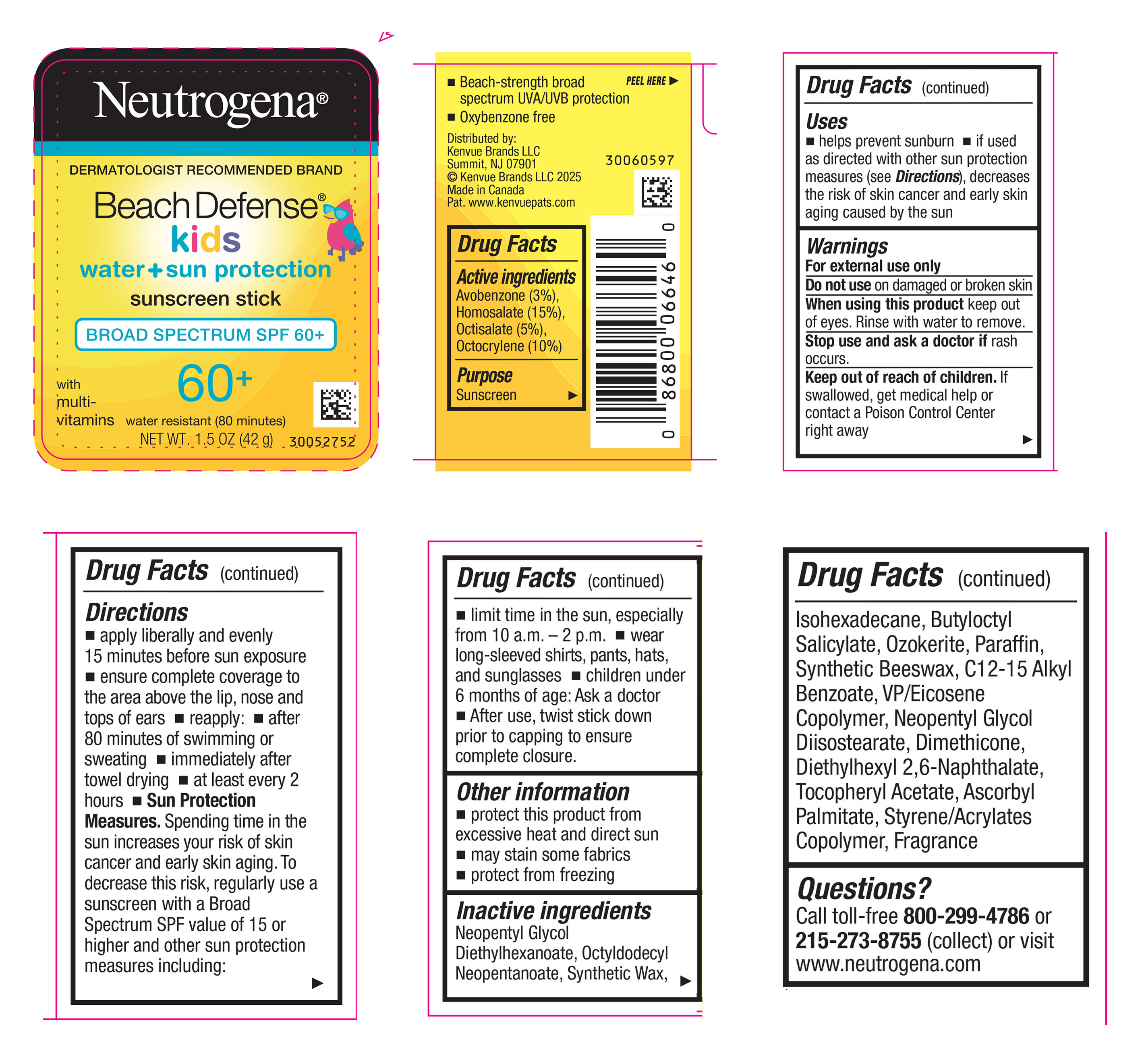 DRUG LABEL: Neutrogena Beach Defense Kids Sunscreen SPF 60 Plus
NDC: 69968-0816 | Form: STICK
Manufacturer: Kenvue Brands LLC
Category: otc | Type: HUMAN OTC DRUG LABEL
Date: 20250707

ACTIVE INGREDIENTS: HOMOSALATE 150 mg/1 g; OCTISALATE 50 mg/1 g; OCTOCRYLENE 100 mg/1 g; AVOBENZONE 30 mg/1 g
INACTIVE INGREDIENTS: OCTYLDODECYL NEOPENTANOATE; ALKYL (C12-15) BENZOATE; DIMETHICONE; ISOHEXADECANE; CERESIN; PARAFFIN; DIETHYLHEXYL 2,6-NAPHTHALATE; SYNTHETIC BEESWAX; NEOPENTYL GLYCOL DIISOSTEARATE; NEOPENTYL GLYCOL DIETHYLHEXANOATE; ALPHA-TOCOPHEROL ACETATE; BUTYLOCTYL SALICYLATE; ASCORBYL PALMITATE; BUTYL METHACRYLATE/METHYL METHACRYLATE/METHACRYLIC ACID/STYRENE CROSSPOLYMER

Neutrogena Beach Defense Kids Sunscreen Stick SPF 60 Plus

Drug Facts

Active ingredients

Avobenzone (3%),

Homosalate (15%),

Octisalate (5%),

Octocrylene (10%)

Purpose

Sunscreen

Uses

▪ helps prevent sunburn

▪ if used as directed with other sun protection measures (see Directions), decreases the risk of skin cancer and early skin aging caused by the sun

Warnings

For external use only

Do not use on damaged or broken skin

- When using this product keep out of eyes. Rinse with water to remove.

Stop use and ask a doctor if rash occurs

Keep out of reach of children. If swallowed, get medical help or contact a Poison Control Center right away

Directions

▪ apply liberally and evenly 15 minutes before sun exposure

▪ ensure complete coverage to the area above the lip, nose and tops of ears

▪ reapply: ▪ after 80 minutes of swimming or sweating ▪ immediately after towel drying

▪ at least every 2 hours

▪ Sun Protection Measures. Spending time in the sun increases your risk of skin cancer and early skin aging. To decrease this risk, regularly use a sunscreen with a Broad Spectrum SPF value of 15 or higher and other sun protection measures including:

▪ limit time in the sun, especially from 10 a.m. – 2 p.m.

▪ wear long-sleeved shirts, pants, hats, and sunglasses

▪ children under 6 months of age: Ask a doctor

▪ After use, twist stick down prior to capping to ensure complete closure.

Other information

- protect this product from excessive heat and direct sun
- may stain some fabrics
- protect from freezing

Inactive ingredients

Neopentyl Glycol Diethylhexanoate, Octyldodecyl Neopentanoate, Synthetic Wax, Isohexadecane, Butyloctyl Salicylate, Ozokerite, Paraffin, Synthetic Beeswax, C12-15 Alkyl Benzoate, VP/Eicosene Copolymer, Neopentyl Glycol Diisostearate, Dimethicone, Diethylhexyl 2,6-Naphthalate, Tocopheryl Acetate, Ascorbyl Palmitate, Styrene/Acrylates Copolymer, Fragrance

Questions?

Call toll-free 800-299-4786 or 215-273-8755 (collect) or visit www.neutrogena.com

Distributed by:
Kenvue Brands LLC
Summit, NJ 07901

PRINCIPAL DISPLAY PANEL - 42 g Canister Label

Neutrogena®

DERMATOLOGIST RECOMMENDED BRAND

Beach Defense®

kids

water + sun protection

sunscreen stick

BROAD SPECTRUM SPF 60+

60+

with

multi-

vitamins

water resistant (80 minutes)

NET WT. 1.5 OZ (42 g)